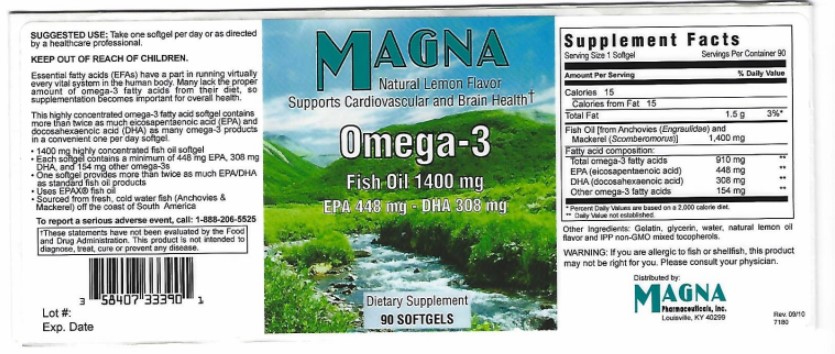 DRUG LABEL: MAGNA Omega 3
NDC: 58407-333 | Form: CAPSULE, GELATIN COATED
Manufacturer: Magna Pharmaceuticals, Inc.
Category: other | Type: DIETARY SUPPLEMENT
Date: 20200917

ACTIVE INGREDIENTS: FISH OIL 1400 mg/1 1
INACTIVE INGREDIENTS: Gelatin; WATER; glycerin; tocopherol; mackerel, unspecified; anchovy, unspecified; LEMON OIL

MAGNA Omega 3

Supplement Facts

Dietary Supplement

Serving Size: 1 Softgel

Servings Per Container: 90

 | Amount Per Serving | % Daily Value
Calories; Calories from Fat; Total Fat Fish Oil (from Anchovies (Engraulidae); and Mackerel (Somberomorus); Fatty Acid Composition Total Omega-3 fatty acids EPA (eicosapentaenoic acid) DHA (doosahexaenoic acid) Other Omega-3 fatty acids | 15; 15; 1.5g; 1400 mg; 910mg; 448mg; 308mg; 154mg | 3%*; **; **; **; **

Other ingredients: Gelatin, glyerin, water, natural lemon oil flavors, and IPP non-GMO mixed tocopherols.

Warning

If you are allergic to fish or shellfish, this product may not be right for you. Please consult your physician.

SAFE HANDLING WARNING

- Keep out of the reach of children.

Purpose

Supports Cardiovascular and Brain Health

PRINCIPAL DISPLAY PANEL - 90 Capsule Bottle Label

MAGNA Omega 3

Dietary Supplement